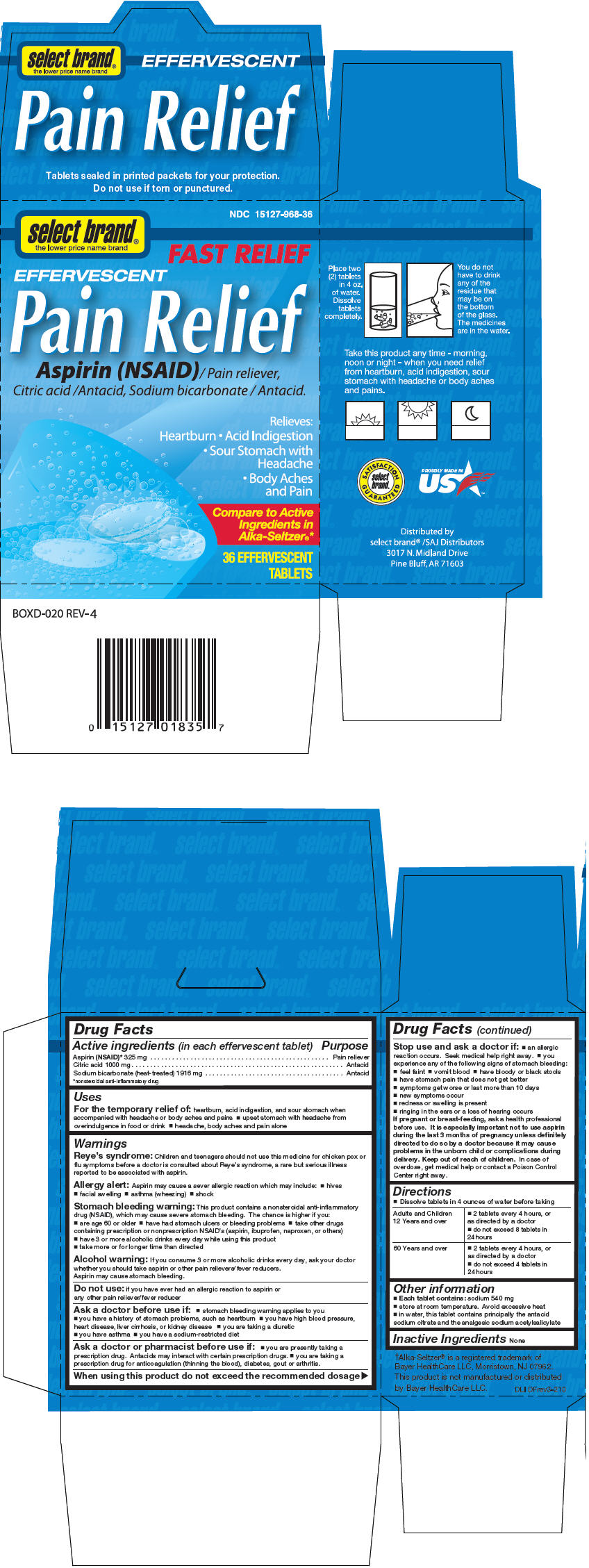 DRUG LABEL: Pain Relief 
NDC: 15127-968 | Form: TABLET, EFFERVESCENT
Manufacturer: Select Brand
Category: otc | Type: HUMAN OTC DRUG LABEL
Date: 20140910

ACTIVE INGREDIENTS: Aspirin 325 mg/1 1; Citric Acid Monohydrate 1000 mg/1 1; Sodium Bicarbonate 1916 mg/1 1

Effervescent Pain Relief
Fast Relief

Drug Facts

ACTIVE INGREDIENT

Active ingredients (in each effervescent tablet) | Purpose
Aspirin (NSAID) [nonsteroidal anti-inflammatory drug] 325 mg | Pain reliever
Citric acid 1000 mg | Antacid
Sodium bicarbonate (heat-treated) 1916 mg | Antacid

Uses

For the temporary relief of: heartburn, acid indigestion, and sour stomach when accompanied with headache or body aches and pains

- upset stomach with headache from overindulgence in food or drink
- headache, body aches and pain alone

Warnings

Reye's syndrome

Children and teenagers should not use this medicine for chicken pox or flu symptoms before a doctor is consulted about Reye's syndrome, a rare but serious illness reported to be associated with aspirin.

Allergy alert

Aspirin may cause a sever allergic reaction which may include:

- hives
- facial swelling
- asthma (wheezing)
- shock

Stomach bleeding warning

This product contains a nonsteroidal anti-inflammatory drug (NSAID), which may cause severe stomach bleeding. The chance is higher if you:

- are age 60 or older
- have had stomach ulcers or bleeding problems
- take other drugs containing prescription or nonprescription NSAID's (aspirin, ibuprofen, naproxen, or others)
- have 3 or more alcoholic drinks every day while using this product
- take more or for longer time than directed

Alcohol warning

If you consume 3 or more alcoholic drinks every day, ask your doctor whether you should take aspirin or other pain relievers/fever reducers.

Aspirin may cause stomach bleeding.

Do not use: if you have ever had an allergic reaction to aspirin or any other pain reliever/fever reducer

Ask a doctor before use if

- stomach bleeding warning applies to you
- you have a history of stomach problems, such as heartburn
- you have high blood pressure, heart disease, liver cirrhosis, or kidney disease
- you are taking a diuretic
- you have asthma
- you have a sodium-restricted diet

Ask a doctor or pharmacist before use if

- you are presently taking a prescription drug. Antacids may interact with certain prescription drugs.
- you are taking a prescription drug for anticoagulation (thinning the blood), diabetes, gout or arthritis.

When using this product do not exceed the recommended dosage

Stop use and ask a doctor if

- an allergic reaction occurs. Seek medical help right away.
- you experience any of the following signs of stomach bleeding:
  - feel faint
  - vomit blood
  - have bloody or black stools
- have stomach pain that does not get better
- symptoms get worse or last more than 10 days
- new symptoms occur
- redness or swelling is present
- ringing in the ears or a loss of hearing occurs

PREGNANCY OR BREAST FEEDING

If pregnant or breast-feeding, ask a health professional before use. It is especially important not to use aspirin during the last 3 months of pregnancy unless definitely directed to do so by a doctor because it may cause problems in the unborn child or complications during delivery.

Keep out of reach of children. In case of overdose, get medical help or contact a Poison Control Center right away.

Directions

- Dissolve tablets in 4 ounces of water before taking

Adults and Children 12 Years and over | - 2 tablets every 4 hours, or as directed by a doctor - do not exceed 8 tablets in 24 hours
60 Years and over | - 2 tablets every 4 hours, or as directed by a doctor - do not exceed 4 tablets in 24 hours

Other information

- Each tablet contains: sodium 540 mg
- store at room temperature. Avoid excessive heat
- in water, this tablet contains principally the antacid sodium citrate and the analgesic sodium acetylsalicylate

Inactive Ingredients

None

Distributed by
select brand® /SAJ Distributors
3017 N. Midland Drive
Pine Bluff, AR 71603

PRINCIPAL DISPLAY PANEL - 36 Tablet Carton

NDC 15127-968-36

select brand®
the lower price name brand

FAST RELIEF

EFFERVESCENT
Pain Relief

Aspirin (NSAID) / Pain reliever,
Citric acid / Antacid, Sodium bicarbonate / Antacid.

Relieves:
Heartburn • Acid Indigestion
• Sour Stomach with
Headache
• Body Aches
and Pain

Compare to Active
Ingredients in
Alka-Seltzer®*

36 EFFERVESCENT
TABLETS